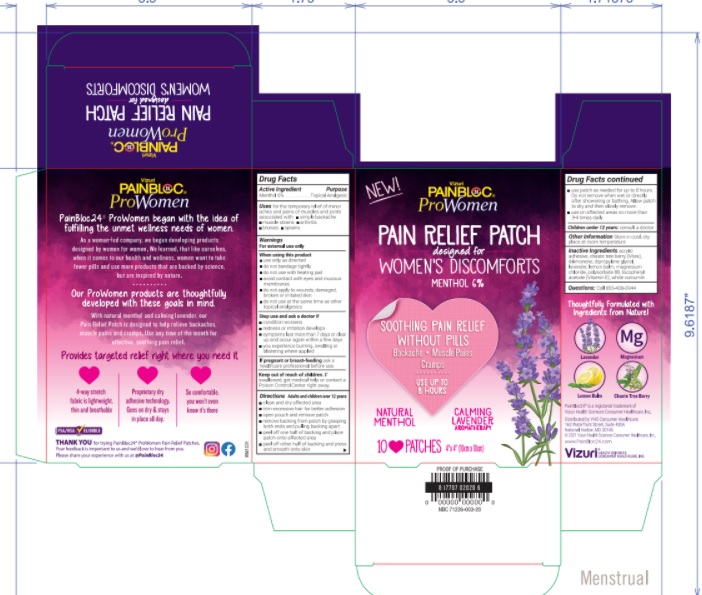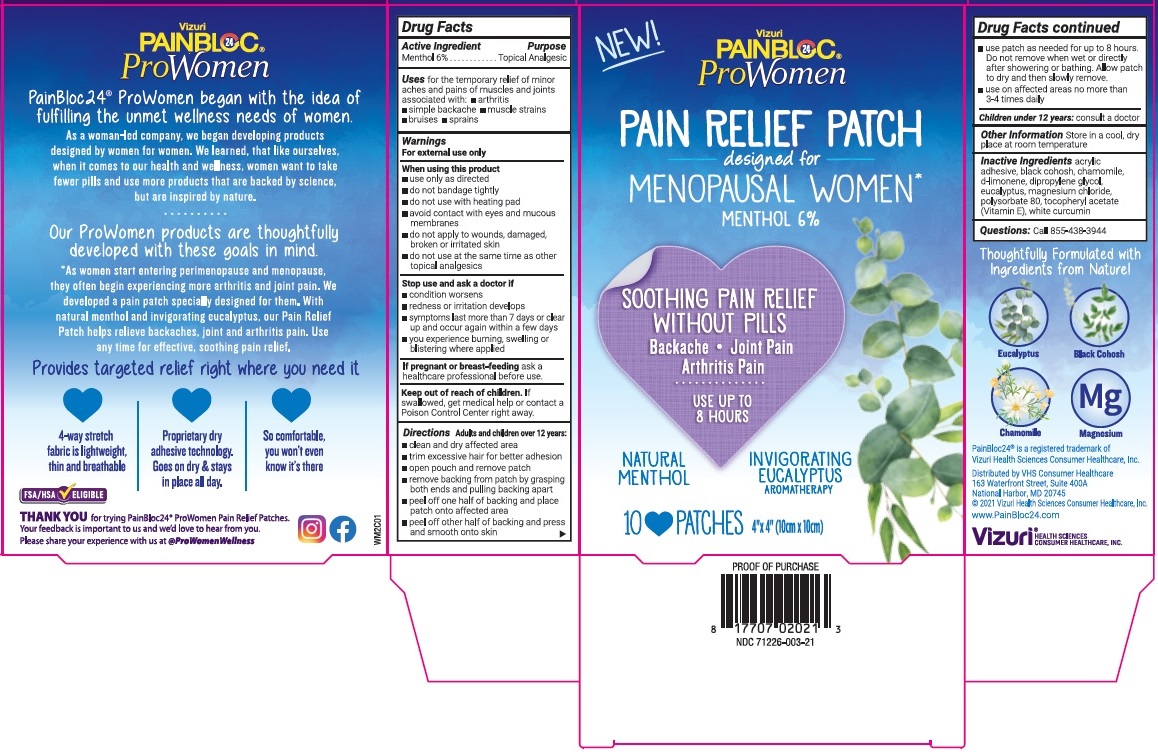 DRUG LABEL: PainBloc24 ProWomen Pain Relief Patch
NDC: 71226-003 | Form: PATCH
Manufacturer: VIZURI HEALTH SCIENCES LLC
Category: otc | Type: HUMAN OTC DRUG LABEL
Date: 20210624

ACTIVE INGREDIENTS: MENTHOL, UNSPECIFIED FORM 6 g/1 1
INACTIVE INGREDIENTS: BLACK COHOSH; CHAMOMILE FLOWER OIL; LIMONENE, (+)-; DIPROPYLENE GLYCOL; EUCALYPTUS OIL; MAGNESIUM CHLORIDE; POLYSORBATE 80; .ALPHA.-TOCOPHEROL ACETATE; CURCUMIN

Active Ingredient

Menthol 6%

Purpose

Topical Analgesic

Uses

for the temporary relief of minor aches and pains of muscles and joints associated with: • arthritis • simple backache • muscle strains • bruises • sprains

Warnings

For external use only

When using this product
• use only as directed
• do not bandage tightly
• do not use with heating pad
• avoid contact with eyes and mucous membranes
• do not apply to wounds, damaged, broken or irritated skin
• do not use at the same time as other topical analgesics

Stop use and ask a doctor if
• condition worsens
• redness or irritation develops
• symptoms last more than 7 days or clear up and occur again within a few days
• you experience burning, swelling or blistering where applied

If pregnant or breast-feeding ask a healthcare professional before use.

Keep out of reach of children. If swallowed, get medical help or contact a Poison Control Center right away.

Directions

Adults and children over 12 years:
• clean and dry affected area
• trim excessive hair for better adhesion
• open pouch and remove patch
• remove backing from patch by grasping both ends and pulling backing apart
• peel off one half of backing and place patch onto affected area
• peel off other half of backing and press and smooth onto skin
• use patch as needed for up to 8 hours. Do not remove when wet or directly after showering or bathing. Allow patch to dry and then slowly remove.
• use on affected area no more than 3-4 times daily

Children under 12 years: consult a doctor

Other Information

Store in a cool, dry place at room temperature

Inactive ingredients

acrylic adhesive, black cohosh, chamomile, d-limonene, dipropylene glycol, eucalyptus, magnesium chloride, polysorbate 80, tocopheryl acetate (Vitamin E), white curcumin

Questions:

Call 855-438-3944

NEW!

designed for MENOPAUSAL WOMEN*

SOOTHING PAIN RELIEF WITHOUT PILLS
Backache • Joint Pain
Arthritis Pain

USE UP TO 8 HOURS

NATURAL MENTHOL

INVIGORATING EUCALYPTUS AROMATHERAPY

Thoughtfully Formulated with Ingredients from Nature!

Eucalyptus

Balck Cohosh

Chamomile

Magnesium

PainBloc24® is a registered trademark of Vizuri Health Sciences Consumer Healthcare, Inc.

Distributed by VHS Consumer Healthcare
163 Waterfront Street, Suite 400A
National Harbor, MD 20745
© 2021 Vizuri Health Sciences Consumer Healthcare, Inc.

www.PainBloc24.com

Vizuri® HEALTH SCIENCES CONSUMER HEALTHCARE, INC.

PainBloc24® ProWomen began with the idea of fulfilling the unmet wellness needs of women.

As a woman-led company, we began developing products designed by women for women. We learned, that like ourselves, when it comes to our health and wellness, women want to take fewer pills and use more products that are backed by science, but are inspired by nature.

Our ProWomen products are thoughtfully developed with these goals in mind.

* As women start entering perimenopause and menopause, they often begin experiencing more arthritis and joint pain. We developed a pain patch specially designed for them. With natural menthol and invigorating eucalyptus, our Pain Relief Patch helps relieve backaches, joint and arthritis pain. Use any time for effective, soothing pain relief.

Provides targeted relief right where you need it

4-way stretch fabric is lightweight, thin and breathable

Proprietary dry adhesive technology. Goes on dry & stays in place all day.

So comfortable, you won't even know it's there

FSA/HSA ELIGIBLE

THANK YOU for trying PainBloc24® ProWomen Pain Relief Patches.
Your feedback is important to us and we'd love to hear from you.
Please share your experience with us at at @ProWomenWellness